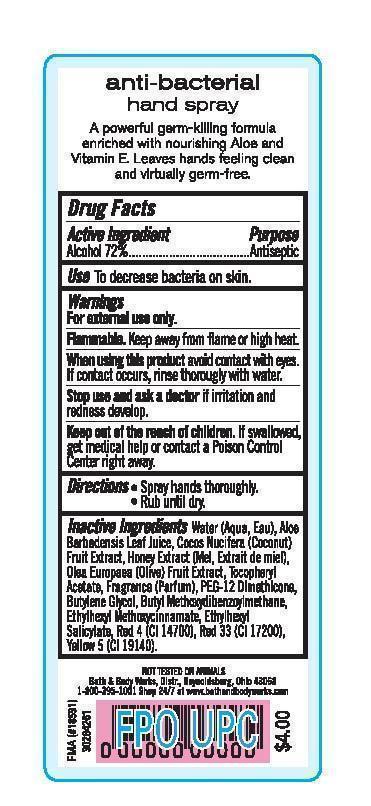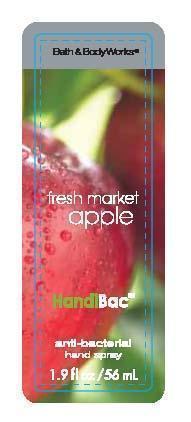 DRUG LABEL: Anti-Bacterial Hand
NDC: 62670-4114 | Form: LIQUID
Manufacturer: Bath & Body Works, Inc.
Category: otc | Type: HUMAN OTC DRUG LABEL
Date: 20150130

ACTIVE INGREDIENTS: ALCOHOL 72 mL/100 mL
INACTIVE INGREDIENTS: WATER

ACTIVE INGREDIENT

Alcohol (72%)

PURPOSE

Antiseptic

USE

To decrease bacteria on skin.

WARNINGS

For external use only.

FLAMMABLE

Keep away from flame or high heat.

WHEN USING THIS PRODUCT

avoid contact with eyes. If contact occurs, rinse thoroughly with water.

STOP USE AND ASK A DOCTOR

if irritation and redness develop.

KEEP OUT OF THE REACH OF CHILDREN

If swallowed, get medical help or contact a Poison Control Center right away.

DIRECTIONS

- Spray hands thoroughly.
- Rub until dry.

INACTIVE INGREDIENTS

Water (Aqua, Eau), Aloe Barbadensis Leaf Juice, Cocos Nucifera (Coconut) Fruit Extract, Honey Extract (Mel, Extrait de miel), Olea Europaea (Olive) Fruit Extract, Tocopheryl Acetate, Fragrance (Parfum), PEG-12 Dimethicone, Butylene Glycol, Butyl Methoxydibenzoylmethane, Ethylhexyl Methoxycinnamate, Ethylhexyl Salicylate, Red 4 (CI 14700), Red 33 (CI 17200), Yellow 5 (CI 19140).

COMPANY INFORMATION

Bath & Body Works, Distr.
Reynoldsburg, Ohio 43068
1-800-395-1001
www.bathandbodyworks.com